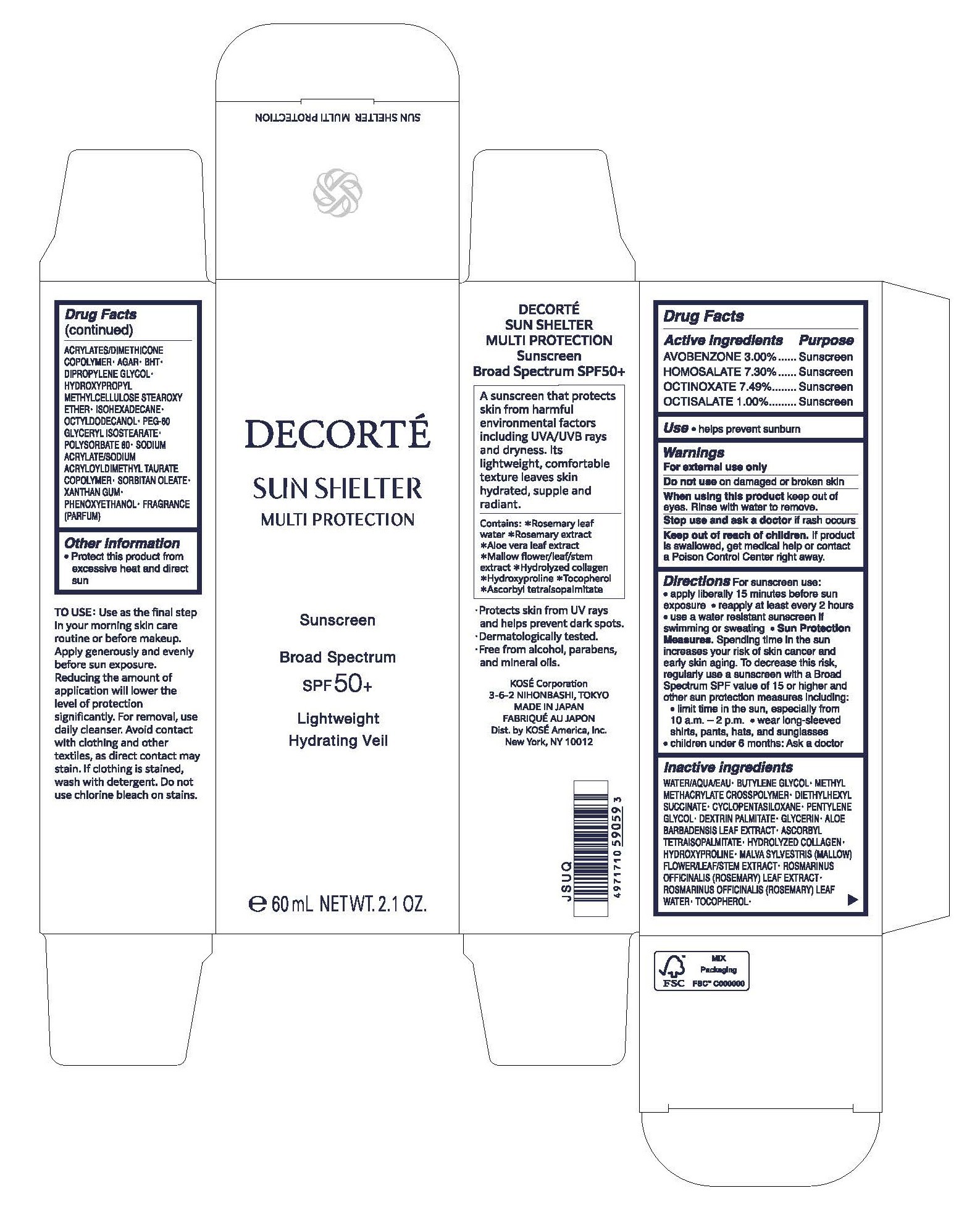 DRUG LABEL: DECORTE SUN SHELTER MULTI PROTECTION Sunscreen SPF 50 Broad Spectrum
NDC: 66820-0600 | Form: LOTION
Manufacturer: KOSÉ America, Inc.
Category: otc | Type: HUMAN OTC DRUG LABEL
Date: 20250415

ACTIVE INGREDIENTS: OCTISALATE 10 mg/1 mL; HOMOSALATE 73 mg/1 mL; OCTINOXATE 74.9 mg/1 mL; AVOBENZONE 30 mg/1 mL
INACTIVE INGREDIENTS: METHYL METHACRYLATE; DIETHYLHEXYL SUCCINATE; CYCLOPENTASILOXANE; PENTYLENE GLYCOL; BUTYLENE GLYCOL; DEXTRIN PALMITATE (CORN; 20000 MW); GLYCERIN; ALOE; ASCORBYL TETRAISOPALMITATE; HYDROXYPROLINE; WATER; MALVA SYLVESTRIS FLOWERING TOP; ROSEMARY; ROSEMARY OIL; TOCOPHEROL; AGAR; BHT; DIPROPYLENE GLYCOL; HYDROXYPROPYL METHYLCELLULOSE; ISOHEXADECANE; OCTYLDODECANOL; PEG-60 GLYCERYL ISOSTEARATE; POLYSORBATE 80; SODIUM ACRYLATE; SORBITAN OLEATE; XANTHAN GUM; PHENOXYETHANOL; FERROSOFERRIC OXIDE; METHYLCELLULOSE

Active Ingredients

Homosalate 7.30% Octisalate 1.00% Avobenzone 3.00% Octinoxate 7.49%

Purpose

Sunscreen

Uses

Helps prevent sunburn

Use as the final step in your morning skin care routine or before makeup. Apply generously and evenly before sun exposure. Reducing the amount of application will lower the level of protection significantly. For removal, use daily cleanser. Avoid contact with clothing and other textiles, as direct contact may stain. If clothing is stained, wash with detergent. Do not use chlorine bleach on stains.

Warnings

For external use only

Do not use on damaged or broken skin.

When using this product keep out of eyes. Rinse with water to remove.

Stop use and ask a doctor if rash occurs.

Keep out of reach of children

If product is swallowed, get medical help or contact a Poison Control Center right away.

Directions

Apply liberally 15 minutes before sun exposure

Use a water resistant sunscreen if swimming or sweating

Reapply at least every 2 hours

Sun Protection Measures

Spending time in the sun increases your risk of skin cancer and early skin aging. To decrease this risk, regularly use a sunscreen with a Broad Spectrum SPF value of 15 or higher and other sun protection measures including.

- limit time in the sun, especially from 10 a.m. -2 p.m. • wear long-sleeved shirts, pants, hats, and sunglasses
- wear long-sleeved shirts, pants, hats, and sunglasses
- children under 6 months: Ask a doctor

Other Information

Protect this product from excessive heat and direct sun.

Protects skin from UV rays and helps prevent dark spots.
Dermatologically tested.
Free from alcohol, parabens, and mineral oils.

Inactive Ingredients

WATER/AQUA/EAU, BUTYLENE GLYCOL, METHYL METHACRYLATE CROSSPOLYMER, DIETHYLHEXYL SUCCINATE, CYCLOPENTASILOXANE, PENTYLENE GLYCOL, DEXTRIN PALMITATE, GLYCERIN, ALOE BARBADENSIS LEAF EXTRACT, ASCORBYL TETRAISOPALMITATE, HYDROLYZED COLLAGEN, HYDROXYPROLINE, MALVA SYLVESTRIS (MALLOW) FLOWER/LEAF/STEM EXTRACT, ROSMARINUS OFFICINALIS (ROSEMARY) LEAF EXTRACT, ROSMARINUS OFFICINALIS (ROSEMARY) LEAF WATER, TOCOPHEROL. ACRYLATES/DIMETHICONE COPOLYMER, AGAR, BHT, DIPROPYLENE GLYCOL, HYDROXYPROPYL METHYLCELLULOSE STEAROXY ETHER, ISOHEXADECANE, OCTYLDODECANOL, PEG-60 GLYCERYL ISOSTEARATE, POLYSORBATE 80, SODIUM ACRYLATE/SODIUM ACRYLOYLDIMETHYL TAURATE COPOLYMER, SORBITAN OLEATE, XANTHAN GUM, PHENOXYETHANOL, FRAGRANCE (PARFUM).

DESCRIPTION

A sunscreen that protects skin from harmful environmental factors including UVA/UVB rays and dryness. Its lightweight, comfortable texture leaves skin hydrated, supple and radiant.

PACKAGE LABEL

PRINCIPAL DISPLAY PANEL - 60 mL
DECORTÉ

SUN SHELTER MULTI PROTECTION

Sunscreen

Broad Spectrum

SPF 50+

Lightweight

Hydrating Veil

e 60 mL NET WT. 2.1 OZ.